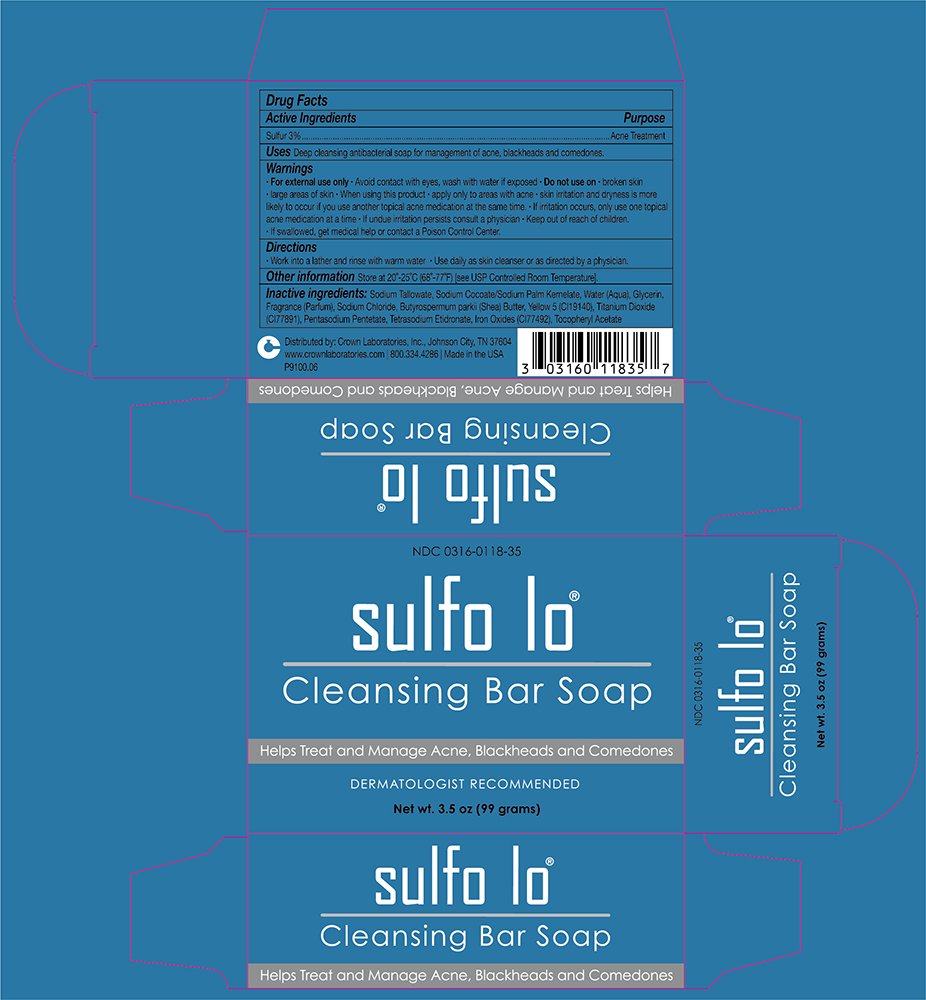 DRUG LABEL: Sulfo lo
NDC: 0316-0118 | Form: SOAP
Manufacturer: Crown Laboratories
Category: otc | Type: HUMAN OTC DRUG LABEL
Date: 20260112

ACTIVE INGREDIENTS: SULFUR 30 mg/1 g
INACTIVE INGREDIENTS: .ALPHA.-TOCOPHEROL ACETATE, D-; SODIUM TALLOWATE, BEEF; SODIUM COCOATE; SODIUM PALM KERNELATE; WATER; GLYCERIN; SODIUM CHLORIDE; PENTASODIUM PENTETATE; ETIDRONATE TETRASODIUM; BROWN IRON OXIDE; TITANIUM DIOXIDE; SHEA BUTTER; BASIC YELLOW 5

Sulfo-Lo Cleansing Bar Soap

Active ingredients

Sulfur 3%

Purpose

Acne Treatment

Uses

Deep cleansing antibacterial soap for management of acne, blackheads and comedones.

Warnings

• For external use only • Avoid contact with eyes, wash with water if exposed

•Do no use on

• broken skin • large areas of skin

• When using this product

• apply only to areas with acne • skin irritation and dryness is more likely to occur if you use another topical acne medication at the same time. • If irritation occurs, only use one topical acne medication at a time • If undue irritation persists consult a physician

• Keep out of reach of children.

• If swallowed, get medical help or contact a Poison Control Center.

Directions

• Work into a lather and rinse with warm water • Use daily as skin cleanser or as directed by a physician.

Other information

Store at 20˚-25˚C (68˚-77˚F) [see USP Controlled Room Temperature].

Inactive ingredients

Sodium Tallowate, Sodium Cocoate/Sodium Palm Kernelate, Water (Aqua), Glycerin, Fragrance (Parfum), Sodium Chloride, Butyrospermum parkii (Shea) Butter, Yellow 5 (CI19140), Titanium Dioxide (CI77891), Pentasodium Pentetate, Tetrasodium Etidronate, Iron Oxides (CI77492), Tocopheryl Acetate

PACKAGE LABEL

NDC 0316-0118-35

sulfo lo®

Cleansing Bar Soap

Helps Treat and Manage Acne, Blackheads and Comedones

DERMATOLOGIST RECOMMENDED

Net wt. 3.5oz (99 grams)

Distributed by: Crown Laboratories, Inc., Johnson City, TN 37604
www.crownlaboratories.com | 800.334.4286 | Made in the USA

P9100.06